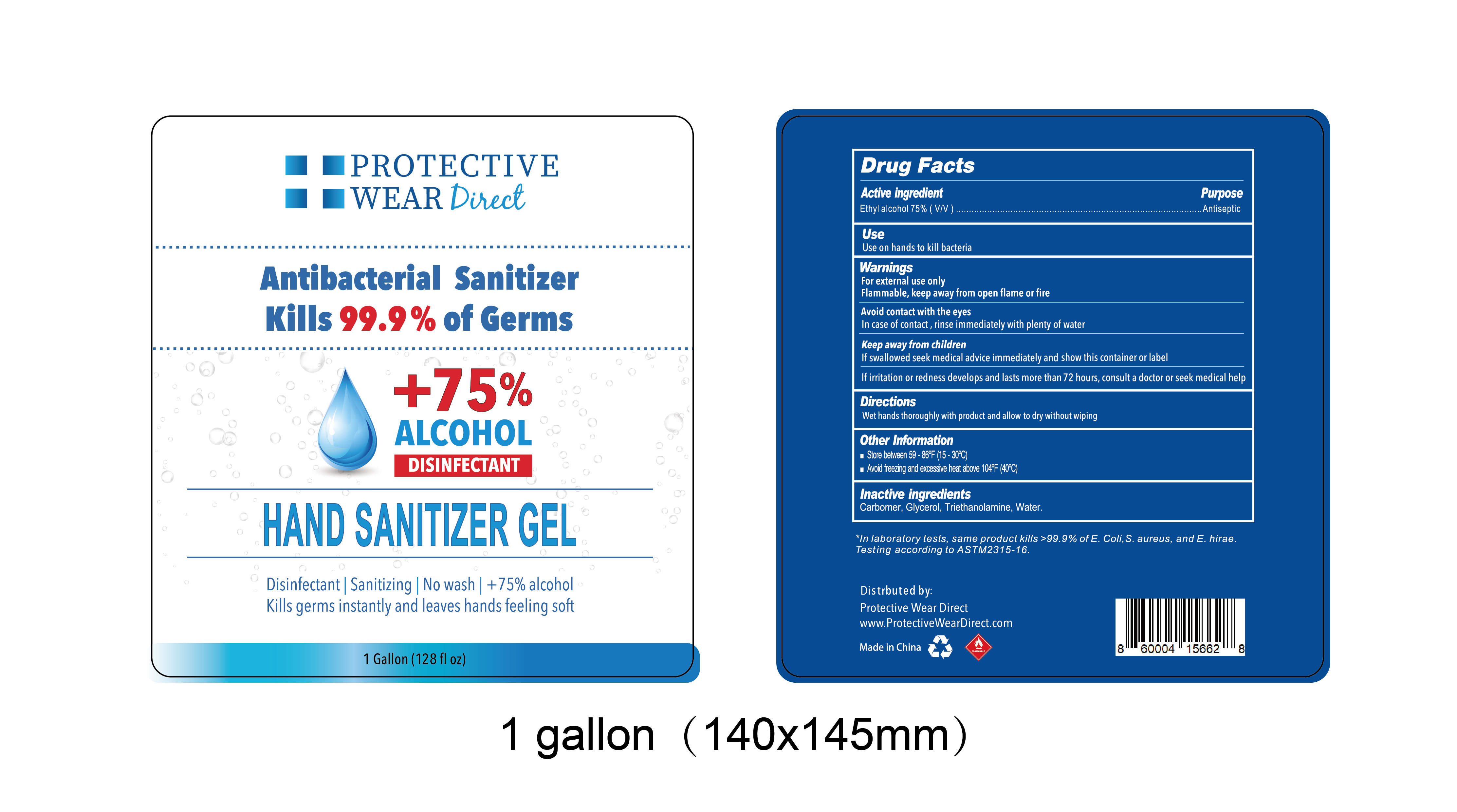 DRUG LABEL: Hand Sanitizer Gel
NDC: 58503-805 | Form: GEL
Manufacturer: China Ningbo Shangge Cosmetic Technology Corp.
Category: otc | Type: HUMAN OTC DRUG LABEL
Date: 20200616

ACTIVE INGREDIENTS: ALCOHOL 75 mL/100 mL
INACTIVE INGREDIENTS: GLYCERIN; CARBOMER HOMOPOLYMER, UNSPECIFIED TYPE; WATER; TROLAMINE

Hand Sanitizer Gel

Active Ingredient(s)

Ethyl Alcohol 75% V/v

Purpose

Antiseptic

Use

Use on hands to kill bacteria

Warnings

For extemal use only. Flammable, Keep away from heat or flame

Do not use

/

WHEN USING

/

STOP USE

/

KEEP OUT OF REACH OF CHILDREN

If swallowed seek medical advice immediately and show this container or label
If irritation or redness develops and lasts more than 72 hours, consult a doctor or seek medical help

Directions

Wet hands thoroughly with product and allow to dry without wiping

Other information

● Store between59-86°F(15-30°c)
● Avoid freezing and excessive heat above104°F(40°c)

Inactive ingredients

Carbomer, Glycerol, Triethanolamine, Water